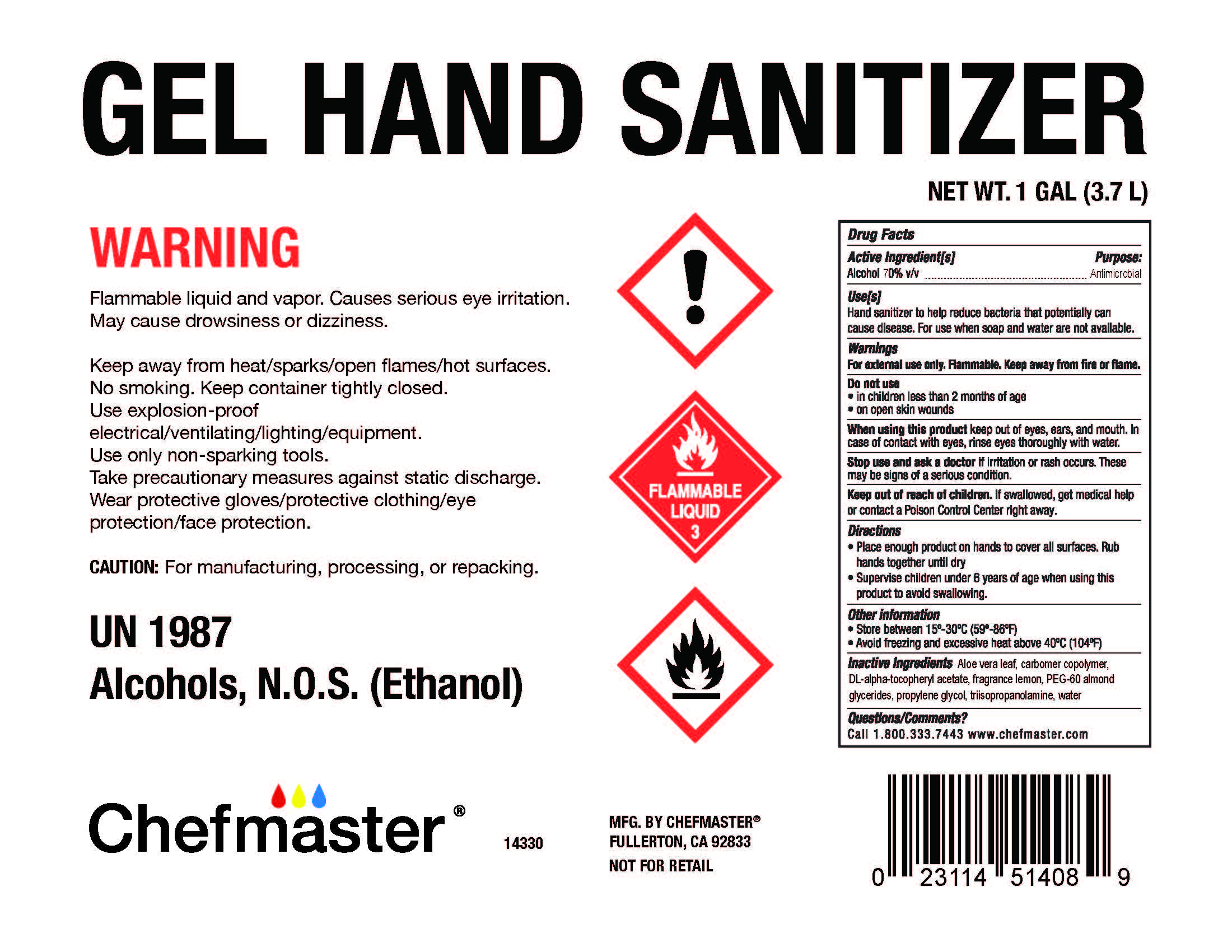 DRUG LABEL: Gel Hand Sanitizer
NDC: 74097-7000 | Form: GEL
Manufacturer: Chefmaster
Category: otc | Type: HUMAN OTC DRUG LABEL
Date: 20201015

ACTIVE INGREDIENTS: ALCOHOL 70 mL/100 mL
INACTIVE INGREDIENTS: CARBOMER COPOLYMER TYPE A 0.42 mL/100 mL; ALOE VERA LEAF 0.0001 mL/100 mL; FRAGRANCE LEMON ORC2001060 0.03 mL/100 mL; TRIISOPROPANOLAMINE 0.3 mL/100 mL; .ALPHA.-TOCOPHEROL ACETATE, DL- 0.0001 mL/100 mL; PEG-60 ALMOND GLYCERIDES 0.3 mL/100 mL; PROPYLENE GLYCOL 0.5 mL/100 mL; WATER 29.4498 mL/100 mL

Active Ingredient(s)

Alcohol 70% v/v. Purpose: Antimicrobial

Purpose

Antiseptic, Hand Sanitizer

Use

Hand Sanitizer to help reduce bacteria that potentially can cause disease. For use when soap and water are not available.

Warnings

For external use only. Flammable. Keep away from heat or flame

Do not use

- in children less than 2 months of age
- on open skin wounds

When using this product keep out of eyes, ears, and mouth. In case of contact with eyes, rinse eyes thoroughly with water.
Stop use and ask a doctor if irritation or rash occurs. These may be signs of a serious condition.
Keep out of reach of children. If swallowed, get medical help or contact a Poison Control Center right away.

Stop use and ask a doctor if irritation or rash occurs. These may be signs of a serious condition.

Keep out of reach of children. If swallowed, get medical help or contact a Poison Control Center right away.

Directions

- Place enough product on hands to cover all surfaces. Rub hands together until dry.
- Supervise children under 6 years of age when using this product to avoid swallowing.

Other information

- Store between 15-30C (59-86F)
- Avoid freezing and excessive heat above 40C (104F)

Inactive ingredients

Aloe vera leaf, carbomer copolymer, DL-alpha-tocopheryl acetate, fragrance lemon, PEG-60 almond glycerides, propylene glycol, triisopropanolamine, water

Package Label - Principal Display Panel

NDC: 74097-7000-1